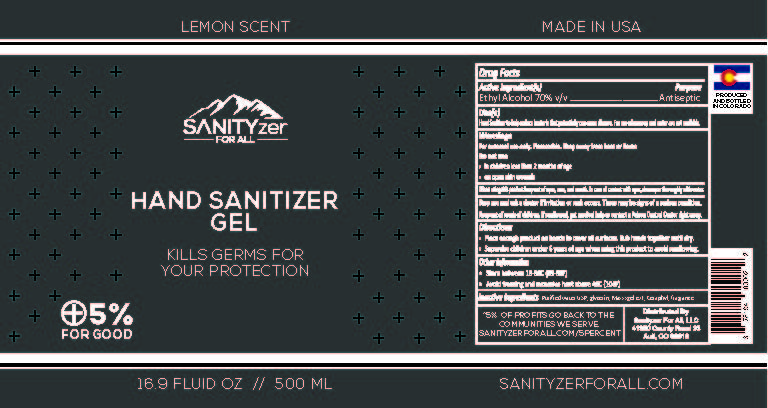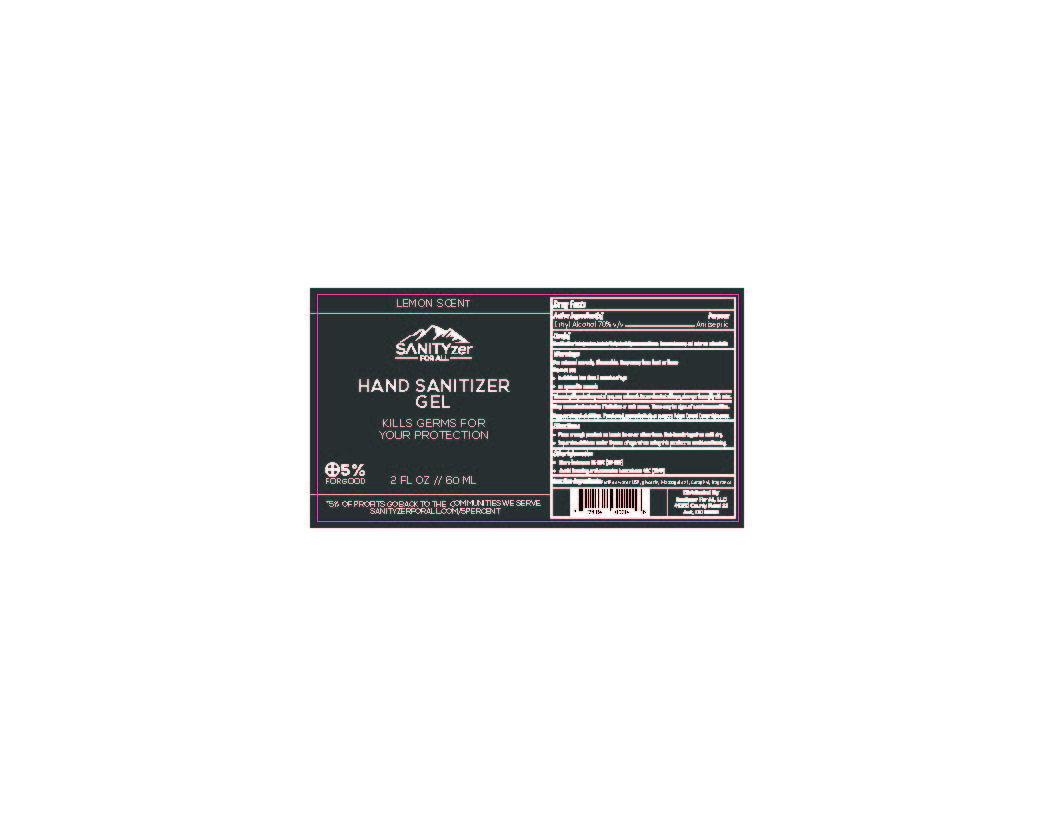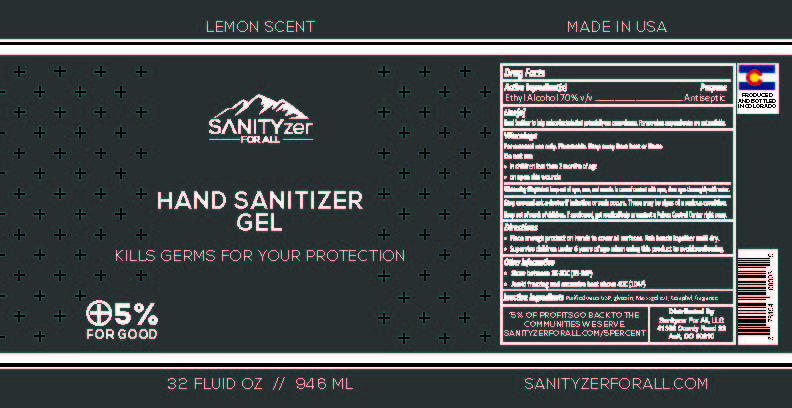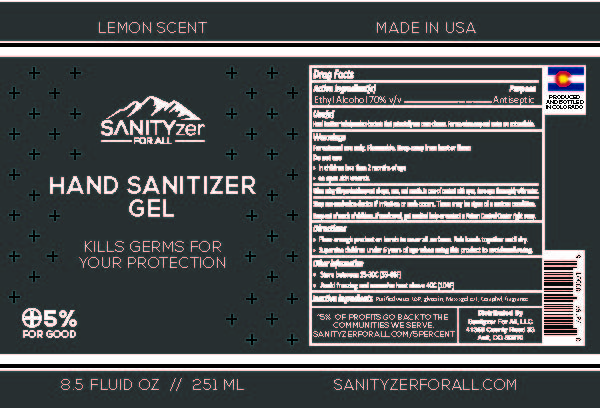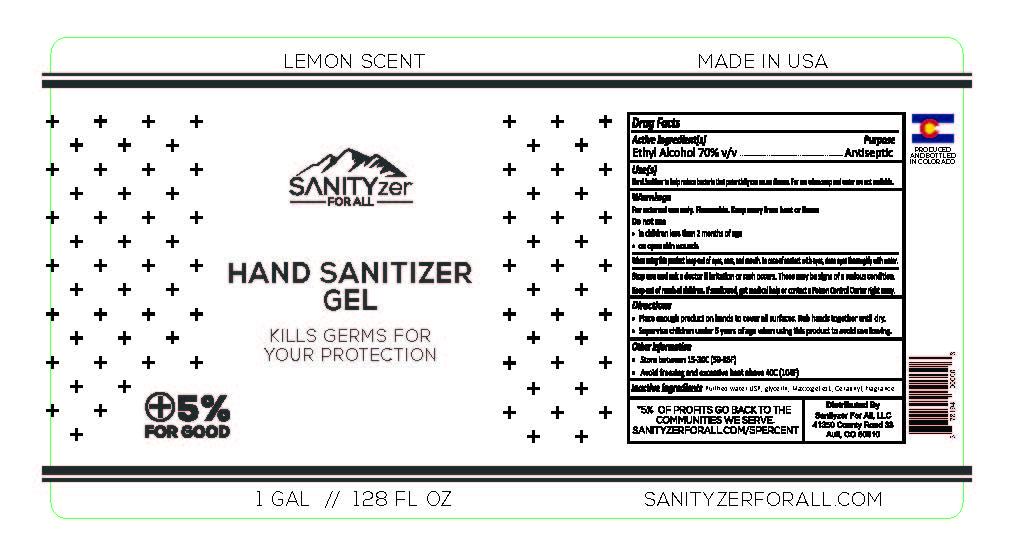 DRUG LABEL: Sanityzer for All
NDC: 78194-000 | Form: GEL
Manufacturer: JB Limited
Category: otc | Type: HUMAN OTC DRUG LABEL
Date: 20200812

ACTIVE INGREDIENTS: ALCOHOL 2650 mL/3785 mL
INACTIVE INGREDIENTS: LAURYL LACTATE; GLYCERIN; WATER; RAPIDGEL EZ1

Sanityzer for All

Active Ingredient

Ethyl alcohol 70%

Purpose

Antiseptic

Uses

Hand Sanitizer to help reduce bacteria that potentially can cause disease. For use when soap and water are not available.

Warnings

For external use only. FLAMMABLE. Keep away from heat or flame

Do not use

In children less than 2 months of age

On open skin wounds

When using this product keep out of eyes, ears, and mouth. In case of contact with eyes, rinse eyes thoroughly with water.

Stop use and ask a doctor if irritation or rash occurs. These may be signs of a serious condition

Keep out of reach of children.

If swallowed, get medical help or contact a Poison Control Center right away.

Directions

Place enough product on hands to cover all surfaces. Rub hands together until dry.

Supervise children under 6 years of age when using this product to avoid swallowing.

Other Information

-Store between 15-30C (59-86F).

-Avoid freezing and excessive heat above 40C (104F)

Inactive Ingredients

Purified Water USP, glycerin, Maxxxgel ez1, Ceraphyl, fragrance